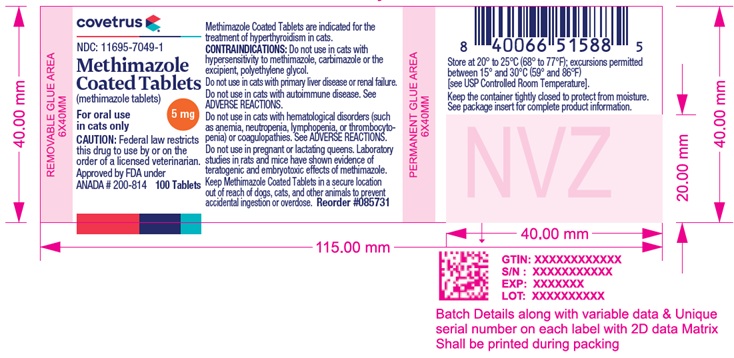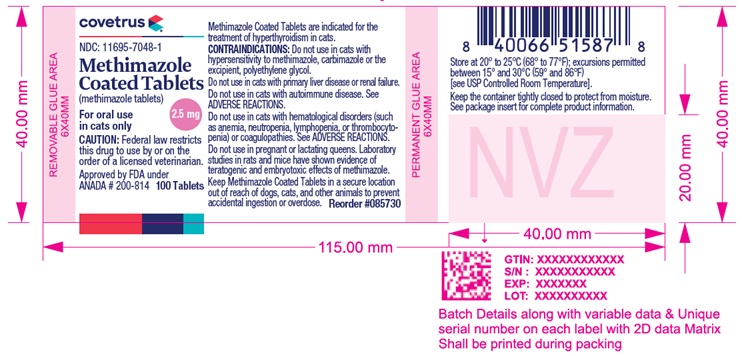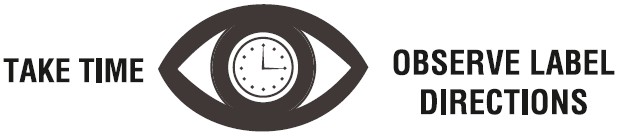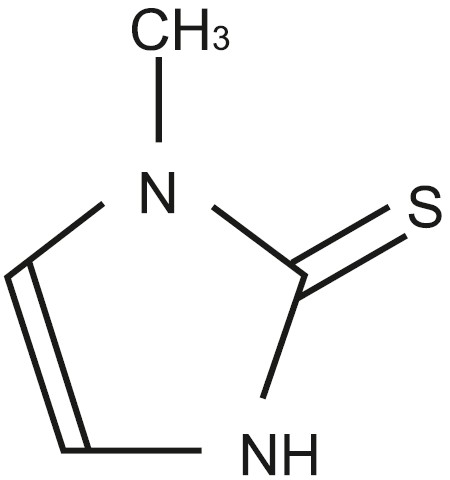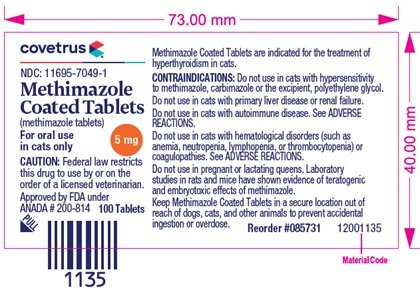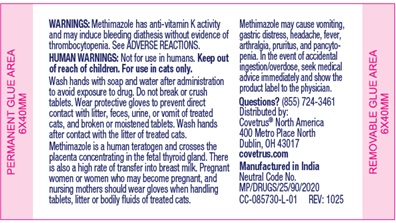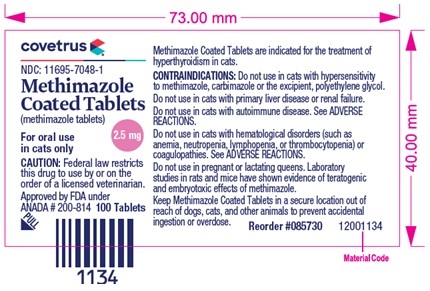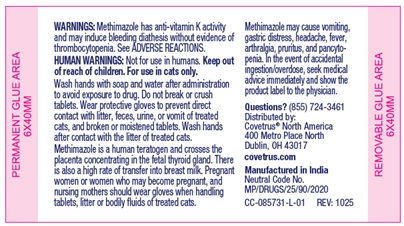 DRUG LABEL: Methimazole
NDC: 11695-7048 | Form: TABLET, COATED
Manufacturer: BUTLER ANIMAL HEALTH SUPPLY, LLC DBA COVETRUS NORTH AMERICA
Category: animal | Type: Prescription Animal Drug Label
Date: 20260115

ACTIVE INGREDIENTS: METHIMAZOLE 2.5 mg/1 1

Methimazole Coated Tablets
(methimazole tablets)
For oral use in cats only.

CAUTION:

Federal law restricts this drug to use by or on the order of a licensed veterinarian.

DESCRIPTION:

Methimazole is a thioureylene antithyroid drug, which inhibits the synthesis of thyroid hormones. Methimazole (1-methylimidazole-2-thiol) is a white, crystalline substance that is freely soluble in water. The chemical formula is C4H6N2S. Molecular weight is 114.16.

Methimazole Chemical Structure:

INDICATION:

Methimazole Coated Tablets (methimazole tablets) are indicated for the treatment of hyperthyroidism in cats.

DOSAGE AND ADMINISTRATION:

The starting dose of Methimazole Coated Tablets is 2.5 mg administered every 12 hours. Following 3 weeks of treatment, the dose should be titrated to effect based on individual serum total T4 (TT4) levels and clinical response. Dose adjustments should be made in 2.5 mg increments. The maximum total dosage is 20 mg per day divided, not to exceed 10 mg as a single administration.

Hematology, biochemistry, and TT4 should be evaluated prior to initiating treatment and monitored after 3 weeks and 6 weeks of treatment. Thereafter, bloodwork should be monitored every 3 months and the dose adjusted as necessary. Cats receiving doses greater than 10 mg per day should be monitored more frequently.

CONTRAINDICATIONS:

Do not use in cats with hypersensitivity to methimazole, carbimazole or the excipient, polyethylene glycol.

Do not use in cats with primary liver disease or renal failure.

Do not use in cats with autoimmune disease. See ADVERSE REACTIONS.

Do not use in cats with hematological disorders (such as anemia, neutropenia, lymphopenia, or thrombocytopenia) or coagulopathies. See ADVERSE REACTIONS.

Do not use in pregnant or lactating queens. Laboratory studies in rats and mice have shown evidence of teratogenic and embryotoxic effects of methimazole.

WARNINGS:

Methimazole has anti-vitamin K activity and may induce bleeding diathesis without evidence of thrombocytopenia. See ADVERSE REACTIONS.

Keep Methimazole Coated Tablets in a secure location out of reach of dogs, cats, and other animals to prevent accidental ingestion or overdose.

HUMAN WARNINGS:

Not for use in humans. Keep out of reach of children. For use in cats only. Wash hands with soap and water after administration to avoid exposure to drug. Do not break or crush tablets. Wear protective gloves to prevent direct contact with litter, feces, urine, or vomit of treated cats, and broken or moistened tablets. Wash hands after contact with the litter of treated cats.

Methimazole is a human teratogen and crosses the placenta concentrating in the fetal thyroid gland. There is also a high rate of transfer into breast milk. Pregnant women or women who may become pregnant, and nursing mothers should wear gloves when handling tablets, litter or bodily fluids of treated cats.

Methimazole may cause vomiting, gastric distress, headache, fever, arthralgia, pruritus, and pancytopenia. In the event of accidental ingestion/overdose, seek medical advice immediately and show the product label to the physician.

PRECAUTIONS:

Use of Methimazole Coated Tablets in cats with renal dysfunction should be carefully evaluated. Reversal of hyperthyroidism may be associated with decreased glomerular filtration rate and a decline in renal function, unmasking the presence of underlying renal disease. Due to potentially serious adverse reactions such as hepatopathy, immune-mediated anemia, thrombocytopenia, and agranulocytosis, cats on methimazole therapy should be monitored closely for any sign of illness including anorexia, vomiting, head/facial pruritus or edema, depression/lethargy, weight loss, anemia, skin lesions, diarrhea, fever, or lymphadenopathy. If a cat becomes ill while on Methimazole Coated Tablets, the drug should be stopped and appropriate hematological and biochemical testing should be done (see ANIMAL SAFETY and POST APPROVAL EXPERIENCE).

Anticoagulants may be potentiated by the anti-vitamin K activity of Methimazole Coated Tablets. Concurrent use of phenobarbital may reduce the clinical effectiveness of Methimazole Coated Tablets. A reduction in dose of certain drugs (β-adrenergic blocking agents, digitalis glycosides, and theophylline) may be needed when the patient becomes euthyroid.

Methimazole is known to reduce the hepatic oxidation of benzimidazole anthelmintics (e.g. fenbendazole), leading to increased plasma concentration of these anthelmintics when administered concurrently. Methimazole tablets caused delayed maturation of the testes in young male cats in the 12-week safety study. See ANIMAL SAFETY. The safety of Methimazole Coated Tablets has not been evaluated in male cats intended for breeding.

ADVERSE REACTIONS:

In a US field study with 113 cats, the most common adverse reactions included change in food consumption (increase or decrease), lethargy, vomiting, diarrhea/loose stool, skin lesions, and abnormal vocalization. Three cats were withdrawn early from the study, one due to unmasking of latent renal disease and two due to the development of skin lesions. Over the course of the study, there was a decreasing trend in the mean counts of red blood cells, lymphocytes, neutrophils and monocytes; however, means remained within or near normal ranges for the testing laboratory.

In the extended use phase of the US field study with 101 cats, the most common adverse reactions reported in the study above (lethargy, anorexia) were also observed. Additional signs occurring more frequently in the long-term study were: depression/withdrawn behavior, weight loss, haircoat abnormalities, increased blood urea nitrogen (BUN), weakness, agitation and diarrhea. Most of the adverse reactions reported were mild and transient.

Serum chemistry and hematology results in the extended use study were consistent with the trends noted during the field study. The mean alanine transaminase (ALT) was above the reference range at the first two quarterly visits, but within the normal reference range (10-100 U/L) through the next two quarterly visits.

Mean lymphocyte counts decreased consistently during the study period, to slightly below the reference range (1200-8000 cells/mcL) at the fourth quarterly visit.

Sixteen cats experienced elevated antinuclear antibody (ANA) titers at one or more points during long-term therapy with methimazole tablets but the significance was not determined. Eighteen cats died or were euthanized during the extended use study, four of which may have been related to methimazole tablets due to the unmasking/acceleration of chronic renal failure. See PRECAUTIONS.

In a foreign field study with 26 cats using a starting dose of 5 mg twice daily (twice the recommended starting dose), one cat was withdrawn due to lethargy, vomiting and facial excoriations. Marked thrombocytopenia was reported in two cats; the platelet count returned to normal in one cat when methimazole tablets were discontinued. Two cats collapsed and died within 12 days of starting methimazole tablets at a dose of 5 mg twice daily. Both cats were reported with lethargy, vomiting, anorexia, and bloody diarrhea; one cat also had pallor.

In a second foreign field study with 78 cats using a starting dose of 2.5 mg twice daily, 4 cats were withdrawn due to suspected adverse reactions to methimazole tablets including anemia, cholangiohepatitis, excoriations, vomiting, lethargy, jaundice, and anorexia. One cat receiving 2.5 mg three times daily collapsed and died after 8 weeks of treatment. Adverse reactions included pallor, anorexia, dehydration, jaundice, bleeding diathesis, and anemia. The most frequently reported adverse reactions included mild, transient, self-limiting vomiting, lethargy, and anorexia.

Foreign Market Experience: The following events were reported voluntarily during post-approval use of methimazole tablets in foreign markets: facial pruritus, self-induced excoriations of the head and neck, generalized lymphadenopathy, thrombocytopenia, hematemesis, epistaxis, and elevation of serum liver enzymes and bilirubin.

If overdosage occurs, stop treatment and give symptomatic and supportive care.

POST APPROVAL EXPERIENCE (revised 2015):

The following adverse events are based on voluntary, post approval reporting. Not all adverse events are reported to FDA/CVM. It is not always possible to reliably estimate the adverse event frequency or establish a causal relationship to product exposure using these data. The following adverse events are listed in decreasing order of reporting frequency: Anorexia, vomiting, head/facial pruritus or edema, depression/lethargy, weight loss, anemia, elevated liver enzymes, skin lesions, elevated BUN, diarrhea, and thrombocytopenia. In some reported cases, the patients recovered after adverse signs were recognized, the drug was withdrawn, and veterinary care was applied. In some cases, death (or euthanasia) has been reported as an outcome of the adverse reactions listed above.

CONTACT INFORMATION:

To report suspected adverse drug experiences, for technical assistance or to obtain a copy of the Safety Data Sheet, contact Covetrus® North America at (855) 724-3461 or covetrus.com. For additional information about adverse drug experience reporting for animal drugs, contact FDA at 1-888-FDA-VETS or http://www.fda.gov/reportanimalae

CLINICAL PHARMACOLOGY:

Methimazole is an antithyroid drug that acts by blocking the biosynthesis of thyroid hormone in vivo. The primary action is to inhibit binding of iodide to the enzyme thyroid peroxidase, thereby preventing the catalyzed iodination of thyroglobulin and T3 and T4 synthesis.

Methimazole Coated Tablets (methimazole tablets) are well absorbed following oral administration. Maximum plasma concentrations are achieved within 1-1½ hours after dosing and methimazole is rapidly eliminated from the blood (T½ is approximately 3 hours). Administration of Methimazole Coated Tablets in a fasted state enhances absorption.

EFFECTIVENESS:

In a US effectiveness field study with 113 cats, the product was considered effective if both the TT4 concentration was ≤ 4.0 mcg/dL, and the Investigator’s clinical assessment documented clinical improvement. Of the 105 evaluable cases, 64 (61%) were considered treatment successes. The decrease in TT4 concentration was significant from the pre-enrollment visit to the Day 42 visit. A TT4 of ≤ 4.0 mcg/dL occurred in 59.1% and 61.9% of cats on Day 21 and Day 42, respectively. Investigators assessed 91.8% and 87.6% of cats as clinically improved on Days 21 and 42, respectively.

In the extended use phase of the US effectiveness field study with 101 cats, effectiveness was based on a combination of Investigator’s clinical assessment, maintenance of TT4 concentrations at or near the laboratory reference range of 0.8-4.0 mcg/dL, and the presence or absence of adverse reactions. Mean TT4 concentrations were within or near the laboratory reference range during the first four quarterly visits. At the first quarterly visit, Investigators categorized 80.9% of cats as stable or improved relative to their baseline assessment. By the fourth quarterly visit, 75.8% were deemed to be stable or improved.

The average maintenance dose required in the extended use phase was 2.5 mg twice daily, with a minimum of 2.5 mg per cat and a maximum of 15 mg per cat on a daily basis.

ANIMAL SAFETY:

ANIMAL SAFETY STUDIES: In a 12-week safety study, healthy young cats were dosed with 0, 10, 20, and 30 mg methimazole tablets per day, divided into two doses. Cats in all treated groups experienced anorexia, vomiting, loose stool and lethargy. Cats in the 20 and 30 mg/day groups also had facial excoriations, pruritus, and lymphadenopathy. The following hematological changes were seen: neutropenia, lymphopenia, anemia, and thrombocytopenia. The following biochemical changes were seen: increased globulin, increased magnesium, increased blood urea nitrogen, increased creatinine and decreased phosphorus. There was a dose-dependent occurrence of antinuclear antibodies. Most of the clinical pathology changes were mild in nature. One cat dosed with 20 mg/day experienced a six-fold increase in ALT during the study. This cat had loose stool, but was otherwise healthy throughout the study. Hepatomegaly was seen in this cat at necropsy and the histopathological examination was comparable to other treated cats with hepatomegaly and normal ALT.

Gross necropsy findings in all treated groups included hepatomegaly, thymus atrophy and thyroid hyperplasia and darkening. Some treated males had delayed maturation of the testes.

The 30 mg/day dose was poorly tolerated and resulted in the clinical deterioration and euthanasia of four of the six cats in that group. Two of the cats showed signs of immune-mediated hemolytic anemia, thrombocytopenia and severe clinical deterioration. One had been on the drug for 34 days, the other for 9 weeks. The drug was discontinued in a third cat treated with 30 mg/day while it received supportive care. It was euthanized on day 55 after becoming anorexic. This cat had anemia (HCT 21.6%) and red blood cell agglutination. Necropsy showed inflammation of the muscular layer of the stomach and a small erosion in the stomach. A fourth cat treated with 30 mg/day was euthanized after several days of anorexia when the decision was made to discontinue dosing in this group. All 30 mg/day cats that died had generalized lymphadenopathy. Necropsies revealed reactive lymph nodes and varying degrees of inflammation throughout the body. The remaining 2 cats in the 30 mg/day group were taken off methimazole tablets at week 9 and fully recovered.

STORAGE INFORMATION:

Store at 20° to 25°C (68° to 77°F); excursions permitted between 15° and 30°C (59° and 86°F) [see USP Controlled Room Temperature].

Keep the container tightly closed to protect from moisture.

HOW SUPPLIED:

Methimazole Coated Tablets are available in 2.5 mg or 5 mg in bottles containing 100 tablets.

NDC Number | Tablet Strength | Tablets per Bottle
11695-7048-1 | 2.5 mg | 100
11695-7049-1 | 5 mg | 100

Approved by FDA under ANADA # 200-814

Questions?
(855) 724-3461
Distributed by:
Covetrus® North America
400 Metro Place North
Dublin, OH 43017
covetrus.com

Manufactured in India
Neutral Code No. MP/DRUGS/25/90/2020
REV: 1025

PACKAGE LABEL.PRINCIPAL DISPLAY PANEL

NDC: 11695-7048-1

100 Tablets

Methimazole Coated Tablets
(methimazole tablets)

2.5 mg

CAUTION: Federal law restricts this drug to use by or on the order of a licensed veterinarian.

Approved by FDA under ANADA # 200-814

Top Layer (Front)

Top Layer (Reverse)

Base Layer

PACKAGE LABEL.PRINCIPAL DISPLAY PANEL

NDC: 11695-7049-1

100 Tablets

Methimazole Coated Tablets
(methimazole tablets)

5 mg

CAUTION: Federal law restricts this drug to use by or on the order of a licensed veterinarian.

Approved by FDA under ANADA # 200-814

Top Layer (Front)

Top Layer (Reverse)

Base Layer